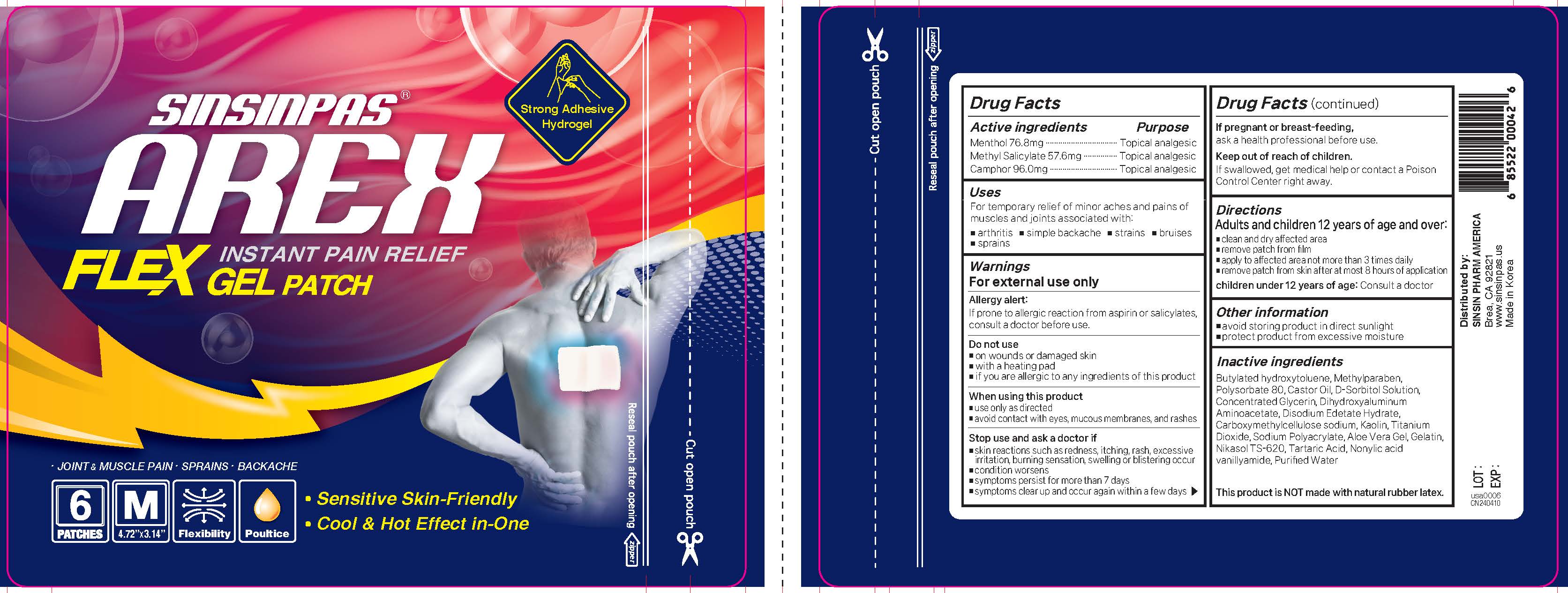 DRUG LABEL: Sinsinpas Arex Flex Gel Pain Relieving Patch
NDC: 55264-116 | Form: PATCH
Manufacturer: Sinsin Pharmaceutical Co., Ltd.
Category: otc | Type: HUMAN OTC DRUG LABEL
Date: 20251007

ACTIVE INGREDIENTS: METHYL SALICYLATE 57.6 mg/1 1; CAMPHOR (SYNTHETIC) 96 mg/1 1; LEVOMENTHOL 76.8 mg/1 1
INACTIVE INGREDIENTS: METHYLPARABEN; EDETATE DISODIUM; TARTARIC ACID; CARBOXYMETHYLCELLULOSE SODIUM; SORBITOL; GELATIN; CASTOR OIL; SODIUM POLYACRYLATE (8000 MW); NONIVAMIDE; GLYCERYL MONOSTEARATE; ALOE VERA LEAF; BUTYLATED HYDROXYTOLUENE; WATER; POLYSORBATE 80; TITANIUM DIOXIDE; ALUMINUM HYDROXIDE; KAOLIN

Active Ingredients

L-Menthol 76.8mg

Methyl Salicylate 57.6mg

DL-Camphor 96.0mg

Purpose

Topical Analgesic

INDICATIONS AND USAGE

For the temporary relief of minor aches and pains of muscles and joints associated with:

- Arthritis
- Simple backache
- Strains
- Bruises
- Sprains

WARNINGS

For external use only

Allergy alert:If prone to allergic reaction from aspirin or salicylates, consult a doctor before use.

Do not use

- on wounds or damaged skin
- if you are allergic to any ingredients of this product
- with a heating pad

When using this product

- use only as directed
- avoid contact with eyes, mucous membranes, and rashes

Stop use and ask a doctor if

- skin reactions such as redness, itching, rash, excessive irritation, burning sensation, swelling or blistering occur
- condition worsens
- symptoms persist for longer than 7 days
- symptoms clear up and reoccur within a few days

If pregnant or breast-feeding, ask a health professional before use.

Keep out or reach of children

Keep out of reach of children.

If swallowed, get medical help or contact a Poison Control Center right away.

Directions

Adults and children 12 years of age and over:

■ clean and dry affected area
■ remove patch from film
■ apply to affected area not more than 3 times daily
■ remove patch from skin after at most 8 hours of application

children under 12 years of age:Consult a doctor

Other Information

■ avoid storing product in direct sunlight
■ protect product from excessive moisture

Inactive Ingredients

Butylated hydroxytoluene, Methylparaben, Polysorbate 80, Castor Oil, D-Sorbitol Solution,
Concentrated Glycerin, Dihydroxyaluminum, Aminoacetate, Disodium Edetate Hydrate, Carboxymethylcellulose sodium, Kaolin, Titanium Dioxide, Sodium Polyacrylate, Aloe Vera Gel, Gelatin, Nikasol TS-620, Tartaric Acid, Nonylic acid vanillyamide, Purified Water